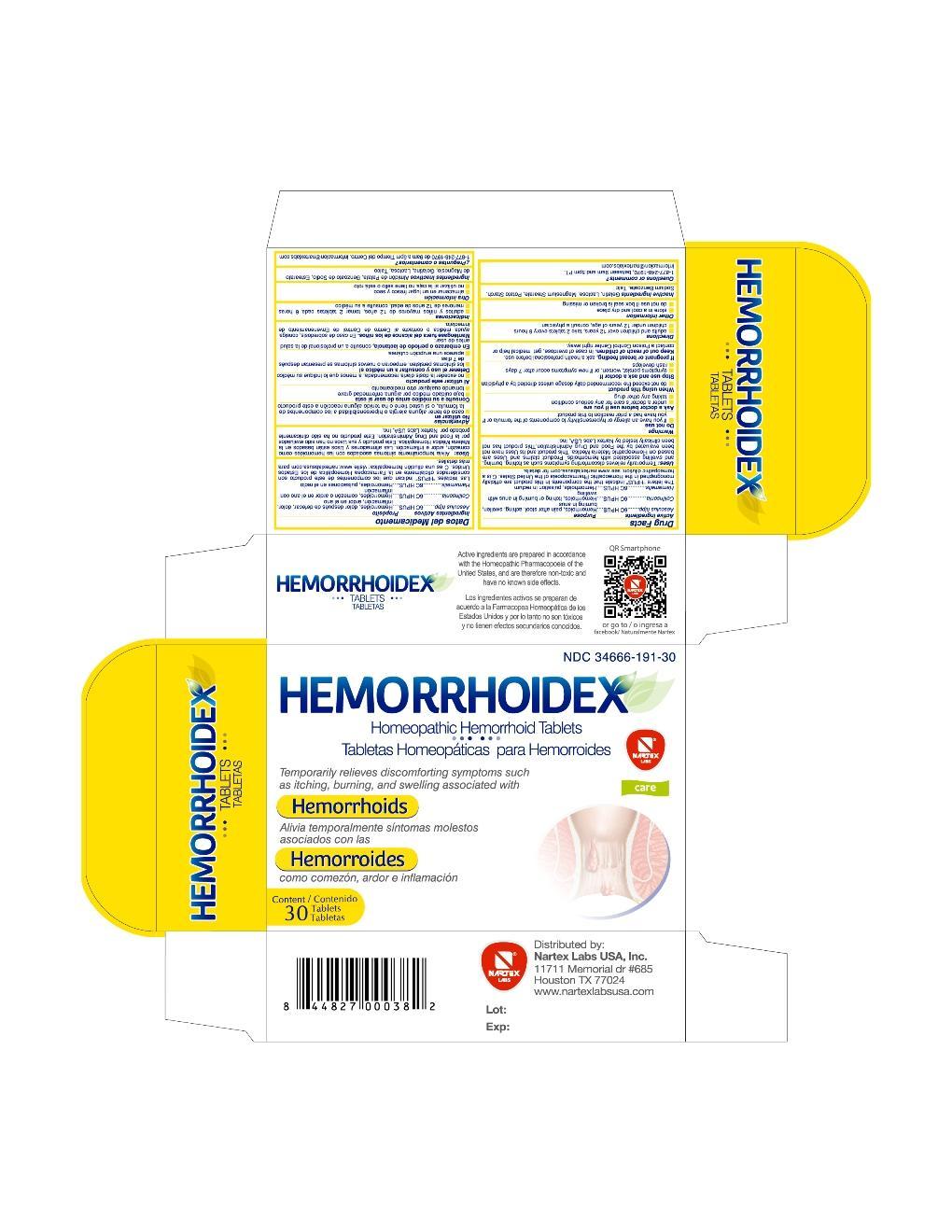 DRUG LABEL: Hemorrhoidex
NDC: 34666-191 | Form: TABLET
Manufacturer: Nartex Laboratorios Homeopaticos SA DE CV
Category: homeopathic | Type: HUMAN OTC DRUG LABEL
Date: 20180227

ACTIVE INGREDIENTS: HORSE CHESTNUT 6 [hp_C]/1 1; COLLINSONIA CANADENSIS ROOT 6 [hp_C]/1 1; HAMAMELIS VIRGINIANA ROOT BARK/STEM BARK 6 [hp_C]/1 1
INACTIVE INGREDIENTS: GELATIN; LACTOSE; MAGNESIUM STEARATE; STARCH, POTATO; SODIUM BENZOATE; TALC

Drug Facts

Active ingredients

Aesculus hipp......6C HPUS

Collinsonia...........6C HPUS

Hamamelis..........6C HPUS

Purpose

Aesculus hipp......6C HPUS....................Hemorrhoids, pain after stool, aching, swollen, burning in anus
Collinsonia...........6C HPUS....................Hemorrhoids, itching or burning in anus with swelling
Hamamelis..........6C HPUS.....................Hemorrhoids, pulsation in rectum

The letters "HPUS" indicate that the components in this product are officially monographed in the Homeopathic Pharmacopoeia of the United States. C is a homeopathic dilution: see www.nartexlabusa.com for details.

Uses

Temporarily relieves discomforting symptoms such as itching, burning, and swelling associated with hemorrhoids. Product claims and Uses have not been evaluated by the Food and Drug Administration. This product has not been clinically tested by Nartex Labs USA, Inc.

Warnings

Do not use

- if you have an allergy or hypersensitivity to components of the formula or if you have had a prior reaction to this product.

Ask a doctor before use if you are

- under a doctor's care for any serious condition
- taking any other drug

When using this product

- do not exceed the recommended daily dosage unless directed by a physician

Stop use and ask a doctor if

- symptoms persist, worsen, or if new symptoms occur after 7 days
- rash develops

PREGNANCY OR BREAST FEEDING

If pregnant or breast feeding, ask a health professional before use.

Keep out of reach of children. In case of overdose, get medical help or contact a Poison Control Center right away.

Directions

- adults and children over 12 years, take 2 tablets every 6 hours
- children under 12 years of age, consult a physician

Other information

- store in a cool and dry place
- do not use if box seal is broken or missing

Inactive Ingredients

Gelatin, Lactose, Magnesium Stearate, Potato Starch, Sodium Benzoate, Talc

Questions or comments?

1-877-248-1970, between 9am and 5pm PT. informacion@nartexlabs.com

PACKAGE LABEL

Hemorrhoidex

Homeopathic Hemorrhoid Tablets

Temporarily relieves discomforting symptoms such as itching, burning, and swelling associated with hemorrhoids

30 Tablets